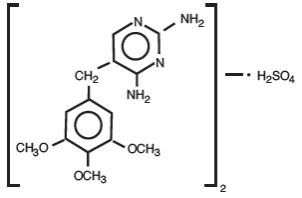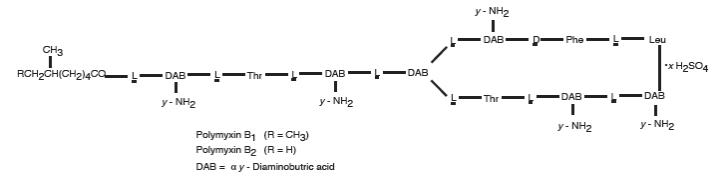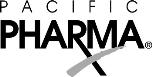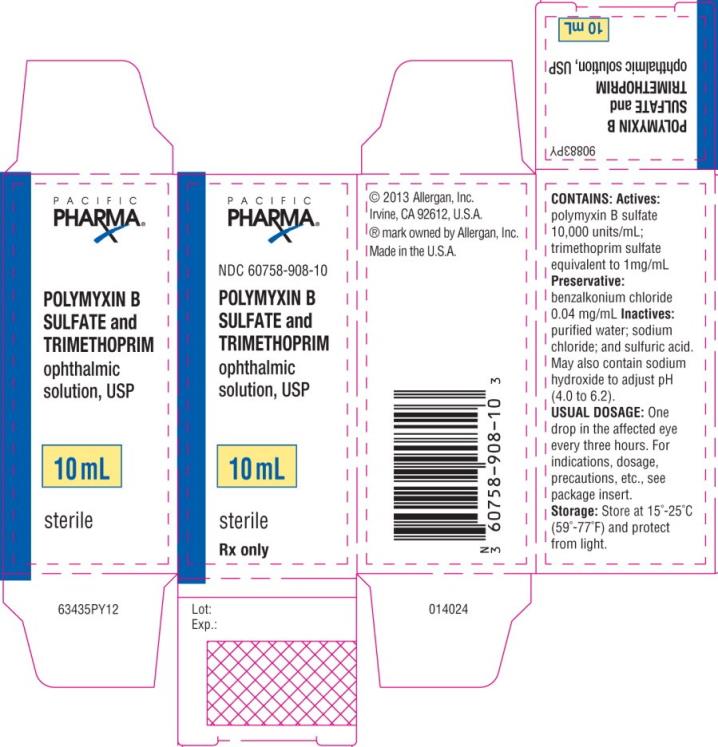 DRUG LABEL: POLYMYXIN B SULFATE and TRIMETHOPRIM SULFATE
NDC: 67296-0850 | Form: SOLUTION/ DROPS
Manufacturer: RedPharm Drug
Category: prescription | Type: HUMAN PRESCRIPTION DRUG LABEL
Date: 20240815

ACTIVE INGREDIENTS: POLYMYXIN B SULFATE 10000 [USP'U]/1 mL; TRIMETHOPRIM SULFATE 1 mg/1 mL
INACTIVE INGREDIENTS: BENZALKONIUM CHLORIDE; WATER; SODIUM CHLORIDE; SULFURIC ACID; SODIUM HYDROXIDE

POLYMYXIN B SULFATE and TRIMETHOPRIM
ophthalmic solution, USP
sterile

DESCRIPTION

Polymyxin B sulfate and trimethoprim ophthalmic solution, USP is a sterile antimicrobial solution for topical ophthalmic use.

Chemical Names:Trimethoprim sulfate, 2,4-Diamino-5-(3,4,5-trimethoxybenzyl) pyrimidine sulfate (2:1), is a white, odorless, crystalline powder with a molecular weight of 678.72 and the following structural formula:

Polymyxin B sulfate is the sulfate salt of polymyxin B1and B2which are produced by the growth of Bacilluspolymyxa (Prazmowski) Migula (Fam. Bacillaceae). It has a potency of not less than 6,000 polymyxin B units per mg, calculated on an anhydrous basis. The structural formulae are:

Contains: Actives:polymyxin B sulfate 10,000 units/mL; trimethoprim sulfate equivalent to 1 mg/mL.

Preservative:benzalkonium chloride 0.04 mg/mL. Inactives:purified water; sodium chloride; and sulfuric acid. May also contain sodium hydroxide for pH adjustment. It has pH of 4.0 to 6.2 and osmolality of 270 to 310 mOsm/kg.

CLINICAL PHARMACOLOGY

Trimethoprim is a synthetic antibacterial drug active against a wide variety of aerobic gram-positive and gram-negative ophthalmic pathogens. Trimethoprim blocks the production of tetrahydrofolic acid from dihydrofolic acid by binding to and reversibly inhibiting the enzyme dihydrofolate reductase. This binding is stronger for the bacterial enzyme than for the corresponding mammalian enzyme, and therefore, selectively interferes with bacterial biosynthesis of nucleic acids and proteins.

Polymyxin B, a cyclic lipopeptide antibiotic, is bactericidal for a variety of gram-negative organisms, especially Pseudomonas aeruginosa. It increases the permeability of the bacterial cell membrane by interacting with the phospholipid components of the membrane.

Blood samples were obtained from 11 human volunteers at 20 minutes, 1 hour and 3 hours following instillation in the eye of 2 drops of ophthalmic solution containing 1 mg trimethoprim and 10,000 units polymyxin B per mL. Peak serum concentrations were approximately 0.03 mcg/mL trimethoprim and 1 unit/mL polymyxin B.

Microbiology

In vitrostudies have demonstrated that the anti-infective components of polymyxin B sulfate and trimethoprim ophthalmic solution, USP are active against the following bacterial pathogens that are capable of causing external infections of the eye:

Trimethoprim: Staphylococcus aureusand Staphylococcus epidermidis, Streptococcus pyogenes, Streptococcus faecalis, Streptococcus pneumoniae, Haemophilusinfluenzae, Haemophilus aegyptius, Escherichia coli, Klebsiella pneumoniae, Proteus mirabilis(indole-negative) , Proteus vulgaris(indole-positive) , Enterobacter aerogenesand Serratia marcescens.

Polymyxin B: Pseudomonas aeruginosa, Escherichia coli, Klebsiella pneumoniae, Enterobacter aerogenes and Haemophilusinfluenzae.

INDICATIONS AND USAGE

Polymyxin B sulfate and trimethoprim ophthalmic solution, USP is indicated in the treatment of surface ocular bacterial infections, including acute bacterial conjunctivitis, and blepharoconjunctivitis, caused by susceptible strains of the following microorganisms: Staphylococcus aureus, Staphylococcus epidermidis, Streptococcus pneumoniae, Streptococcusviridans, Haemophilusinfluenzae and Pseudomonas aeruginosa.*

*Efficacy for this organism in this organ system was studied in fewer than 10 infections.

CONTRAINDICATIONS

Polymyxin B sulfate and trimethoprim ophthalmic solution, USP is contraindicated in patients with known hypersensitivity to any of its components.

WARNINGS

NOT FOR INJECTION INTO THE EYE. If a sensitivity reaction to polymyxin B sulfate and trimethoprim ophthalmic solution, USP occurs discontinue use. Polymyxin B sulfate and trimethoprim ophthalmic solution, USP is not indicated for the prophylaxis or treatment of ophthalmia neonatorum.

PRECAUTIONS

General

As with other antimicrobial preparations, prolonged use may result in overgrowth of nonsusceptible organisms, including fungi. If superinfection occurs, appropriate therapy should be initiated.

Information for Patients

Avoid contaminating the applicator tip with material from the eye, fingers, or other source. This precaution is necessary if the sterility of the drops is to be maintained.

If redness, irritation, swelling or pain persists or increases, discontinue use immediately and contact your physician.

Patients should be advised not to wear contact lenses if they have signs and symptoms of ocular bacterial infections.

Carcinogenesis, Mutagenesis, Impairment of Fertility

Carcinogenesis:Long-term studies in animals to evaluate carcinogenic potential have not been conducted with polymyxin B sulfate or trimethoprim.

Mutagenesis:Trimethoprim was demonstrated to be non-mutagenic in the Ames assay. In studies at two laboratories no chromosomal damage was detected in cultured Chinese hamster ovary cells at concentrations approximately 500 times human plasma levels after oral administration; at concentrations approximately 1,000 times human plasma levels after oral administration in these same cells, a low level of chromosomal damage was induced at one of the laboratories. Studies to evaluate mutagenic potential have not been conducted with polymyxin B sulfate.

Impairment of Fertility:Polymyxin B sulfate has been reported to impair the motility of equine sperm, but its effects on male or female fertility are unknown.

No adverse effects on fertility or general reproductive performance were observed in rats given trimethoprim in oral dosages as high as 70 mg/kg/day for males and 14 mg/kg/day for females.

Pregnancy:

Teratogenic Effects Animal reproduction studies have not been conducted with polymyxin B sulfate. It is not known whether polymyxin B sulfate can cause fetal harm when administered to a pregnant woman or can affect reproduction capacity.

Trimethoprim has been shown to be teratogenic in the rat when given in oral doses 40 times the human dose. In some rabbit studies, the overall increase in fetal loss (dead and resorbed and malformed conceptuses) was associated with oral doses 6 times the human therapeutic dose.

While there are no large well-controlled studies on the use of trimethoprim in pregnant women, Brumfitt and Pursell, in a retrospective study, reported the outcome of 186 pregnancies during which the mother received either placebo or oral trimethoprim in combination with sulfamethoxazole. The incidence of congenital abnormalities was 4.5% (3 of 66) in those who received placebo and 3.3% (4 of 120) in those receiving trimethoprim and sulfamethoxazole. There were no abnormalities in the 10 children whose mothers received the drug during the first trimester. In a separate survey, Brumfitt and Pursell also found no congenital abnormalities in 35 children whose mothers had received oral trimethoprim and sulfamethoxazole at the time of conception or shortly thereafter.

Because trimethoprim may interfere with folic acid metabolism, trimethoprim should be used during pregnancy only if the potential benefit justifies the potential risk to the fetus.

Nonteratogenic Effects

The oral administration of trimethoprim to rats at a dose of 70 mg/kg/day commencing with the last third of gestation and continuing through parturition and lactation caused no deleterious effects on gestation or pup growth and survival.

Nursing Mothers:

It is not known whether this drug is excreted in human milk. Because many drugs are excreted in human milk, caution should be exercised when polymyxin B sulfate and trimethoprim ophthalmic solution, USP is administered to a nursing woman.

Pediatric Use:

Safety and effectiveness in children below the age of 2 months have not been established (see WARNINGS).

Geriatric Use:

No overall differences in safety or effectiveness have been observed between elderly and other adult patients.

ADVERSE REACTIONS

The most frequent adverse reaction to polymyxin B sulfate and trimethoprim ophthalmic solution, USP is local irritation consisting of increased redness, burning, stinging, and/or itching. This may occur on instillation, within 48 hours, or at any time with extended use. There are also multiple reports of hypersensitivity reactions consisting of lid edema, itching, increased redness, tearing, and/or circumocular rash. Photosensitivity has been reported in patients taking oral trimethoprim.

DOSAGE AND ADMINISTRATION

In mild to moderate infections, instill one drop in the affected eye(s) every three hours (maximum of 6 doses per day) for a period of 7 to 10 days.

HOW SUPPLIED

Polymyxin B sulfate and trimethoprim ophthalmic solution, USP is supplied sterile in opaque white low density polyethylene ophthalmic dispenser bottles and tips with white high impact polystyrene (HIPS) caps as follows:

10 mL in 10 mL bottle - NDC 60758-908-10

Storage:Store at 15°-25°C (59°-77°F) and protect from light.

Rx only

Revised:12/2018

For more information, call 1-800-678-1605

Distributed for
Allergan USA, Inc.
Madison, NJ 07940

© 2019 Allergan, Inc.
All trademarks are the property of their respective owners

v1.0USPI908

PRINCIPAL DISPLAY PANEL

NDC 60758-908-10

POLYMYXIN B
SULFATE and
TRIMETHOPRIM
ophthalmic
solution, USP

10 mL

sterile
Rx only